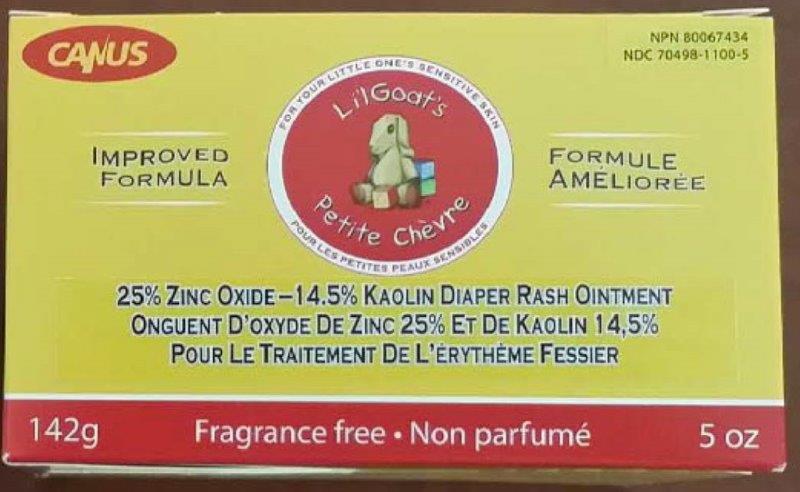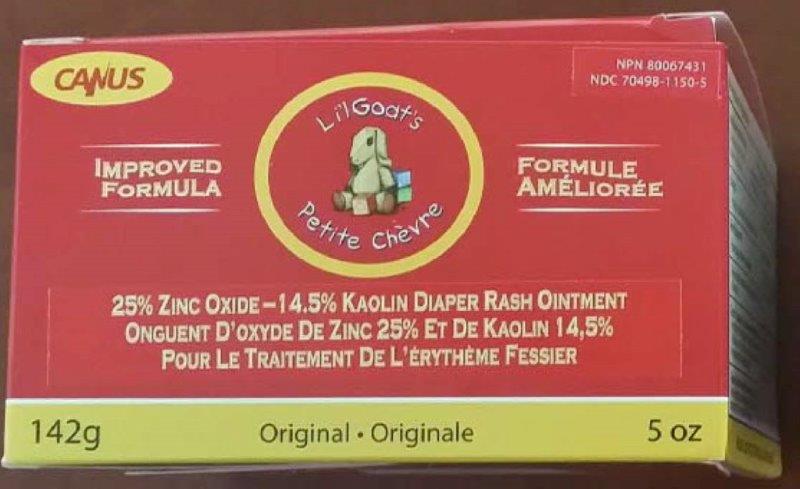 DRUG LABEL: Lil Goats Petite Chevre Original
NDC: 70498-1150 | Form: OINTMENT
Manufacturer: Produits De Soins Pour La Peau Au Lait De Chevre Canus Inc
Category: otc | Type: HUMAN OTC DRUG LABEL
Date: 20211004

ACTIVE INGREDIENTS: KAOLIN 145 mg/1 g; ZINC OXIDE 250 mg/1 g
INACTIVE INGREDIENTS: WHITE WAX; CETOSTEARYL ALCOHOL; GLYCERIN; GOAT MILK; POLYSORBATE 60; PETROLATUM; MINERAL OIL; CAPRYLHYDROXAMIC ACID; CAPRYLYL GLYCOL

Li'l Goat's Petite Chèvre

Active Ingredients

Zinc Oxide 25% w/w

Kaolin 14.5% w/w

Purpose

Skin Protectant

Use

Helps treat and prevent diaper rash.

Warnings

For external use only.

When using this product avoid all contact with eyes.

Stop use and ask and doctor if condition worsens or does not improve within 7 days or clear up and occur again within a few days

Keep out of reach of children. If swallowed, get medical help or contact the Poison Control Center immediately.

Directions

- Change wet and soiled diapers promptly.
- Clean the diaper area and allow to dry.
- Apply ointment liberally as often as necessary with each diaper change.

Other Information

- Store at 20 - 25° C (68 - 77° F).
- Do not use if safety seal is missing or broken.

Inactive Ingredients

Beeswax/Cera Alba, Caprylhydroxamic Acid, Caprylyl Glycol, Cetearyl Alcohol, Glycerin, Caprae Lac/Goat Milk, Mineral Oil, Fragrance (in Original formula only), Petrolatum, Polysorbate 60.

Additional information listing on other panels

Manufactured for:

Canus Goat's Milk Skin Care Products Inc.

Drummondville (Québec) CANADA J2A 0N2

(514) 738-8998

1 Sheila Drive, Tinton Falls, New Jersey USA 07724

(848) 300-2227

www.lilgoats.com

Finished product not tested on animals.

PACKAGE LABEL

Canus

NPN 80067434

NDC 70498-1100-5

Li'l Goat's Petite Chèvre

Improved Formula

25% Zinc Oxide - 14.5% Kaolin Diaper Rash Ointment

Fragrance free

142g

5 oz

Principal Display Panel

Canus

NPN 80067431

NDC 70498-1150-5

Li'l Goat's Petite Chèvre

Improved Formula

25% Zinc Oxide - 14.5% Kaolin Diaper Rash Ointment

Original

142g

5 oz